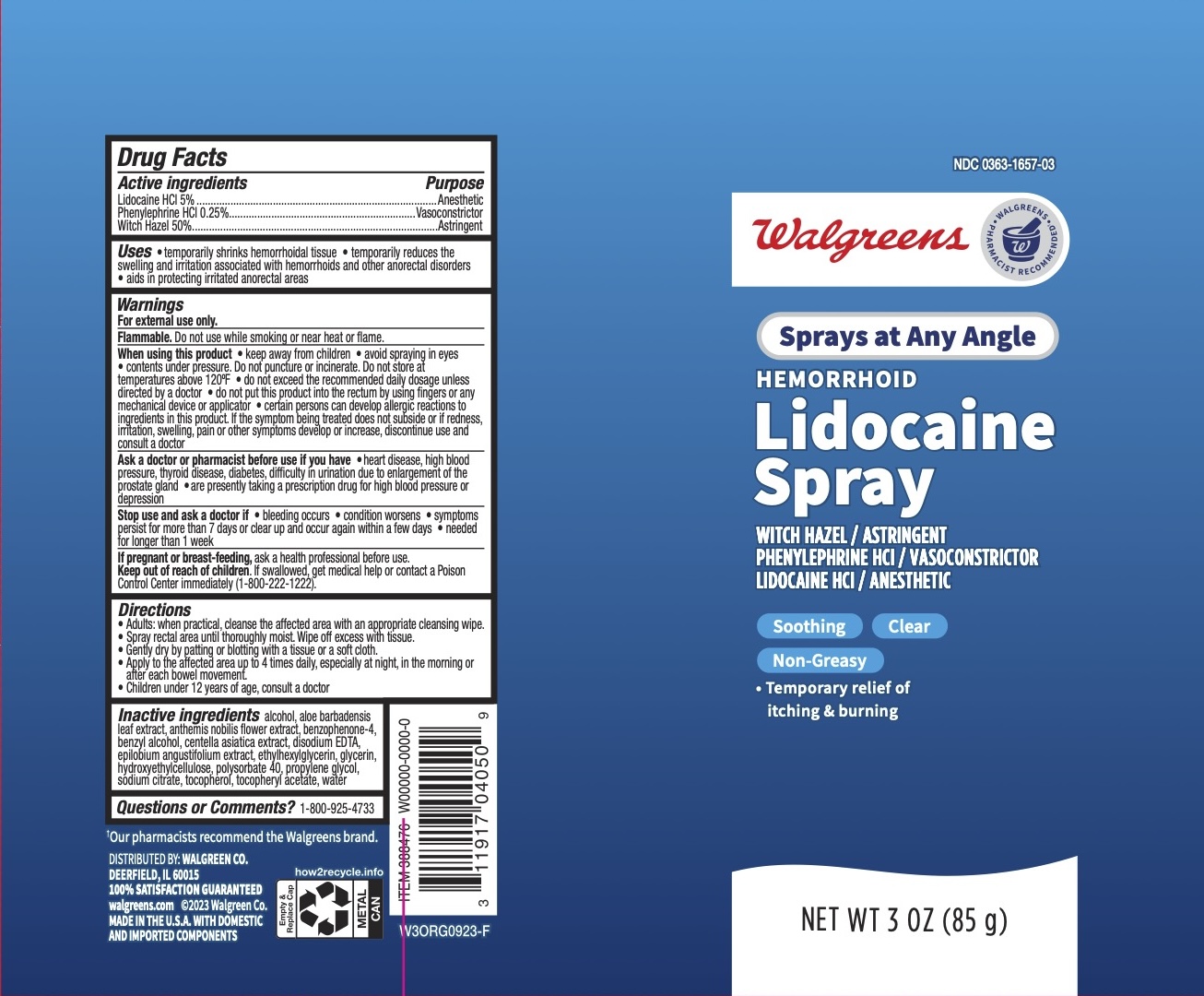 DRUG LABEL: Lidocaine Hemorrhoid
NDC: 0363-1657 | Form: SPRAY
Manufacturer: Walgreens Co
Category: otc | Type: HUMAN OTC DRUG LABEL
Date: 20240205

ACTIVE INGREDIENTS: WITCH HAZEL 50 g/100 g; PHENYLEPHRINE HYDROCHLORIDE 0.25 g/100 g; LIDOCAINE HYDROCHLORIDE ANHYDROUS 5 g/100 g
INACTIVE INGREDIENTS: CENTELLA ASIATICA TRITERPENOIDS; POLYSORBATE 40; SODIUM CITRATE; WATER; SULISOBENZONE; BENZYL ALCOHOL; ALCOHOL; EPILOBIUM ANGUSTIFOLIUM LEAF; .ALPHA.-TOCOPHEROL ACETATE; CHAMAEMELUM NOBILE FLOWER; GLYCERIN; HYDROXYETHYL CELLULOSE, UNSPECIFIED; ETHYLHEXYLGLYCERIN; EDETATE DISODIUM; PROPYLENE GLYCOL; TOCOPHEROL; ALOE VERA LEAF

Walgreens Lidocaine Spray

ACTIVE INGREDIENT

Lidocaine HCl 5%, Phenylephrine HCl 0.25%, Witch Hazel 50%

PURPOSE

Anorectal; anesthetic, vasoconstrictor, astringent

INDICATIONS AND USAGE

- Temporarily shrinks hemorrhoidal tissue
- Temporarily reduces the swelling and irritation associated with hemorrhoids and other anorectal disorders
- aids in protecting irritated anorectal areas

INDICATIONS AND USAGE

Temporarily shrinks hemorrhoidal tissue. Temporarily reduces the swelling and irritation associated with hemorrhoids and other anorectal disorders. Aids in protecting irritated anorectal areas.

WARNINGS

For external use only.

Flammable. Do not use while smoking or near heat or flame.

When using this product

- keep away from children
- avoid spraying in eyes
- contents under pressure. Do not puncture or incinerate. Do not store at temperatures above 120F
- do not exceed the recommended daily dosage unless directed by a doctor
- do not put this product into the rectum by using fingers or any mechanical device or applicator
- certain persons can develop allergic reactions to ingredients in this product. If the symptoms being treated does not subside or if redness, irritation, swelling, pain or other symptoms develop or increase, discontinue use and consult a doctor.

Ask a doctor or pharmacist before use if you have

- heart disease, high blood pressure, thyroid disease, diabetes, difficulty in urination due to enlargement of the prostate gland
- are presently taking a prescription drug for high blood pressure or depression

Stop use and ask a doctor if

- bleeding occurs
- condition worsens
- symptoms persist for more than 7 days or clear up and occur again within a few days
- needed for longer than 1 week

PREGNANCY OR BREAST FEEDING

Ask a health professional before use.

KEEP OUT OF REACH OF CHILDREN

If swallowed, get medical help or contact a Poison Control Center immediately (1-800-222-1222).

DOSAGE AND ADMINISTRATION

- Adults: when practical, cleanse the affected are with an appropriate cleansing wipe.
- Spray rectal area until thoroughly moist. Wipe off excess with tissue.
- Gently dry by patting or blotting with a tissue or a soft cloth.
- Apply to the affected area up to 4 times daily, especially at night, in the morning or after each bowel movement.
- Children under 12 years of age, consult a doctor.

INACTIVE INGREDIENT

alcohol, aloe barbadensis leaf extract, anthemis nobilis flower extract, benzophenone-4, benzyl alcohol, centella asiatica extract,disodium EDTA, epilobium angustifolium extract, ethylhexylglycerin, glycerin, hydroxyethylcellulose, polysorbte 40, propylene glycol, sodium citrate, tocopherol, tocopheryl acetate, water.

QUESTIONS

1-800-925-4733